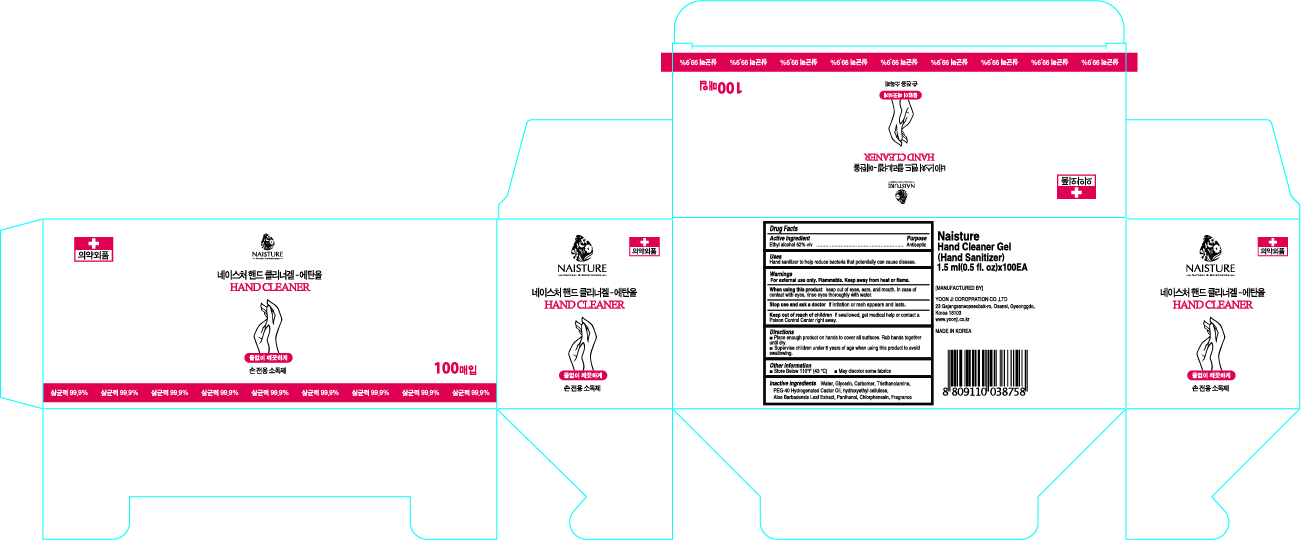 DRUG LABEL: Naisture Hand Cleaner Gel(Hand Sanitizer)
NDC: 75024-015 | Form: GEL
Manufacturer: YOON JI CORPORATION CO.,LTD
Category: otc | Type: HUMAN OTC DRUG LABEL
Date: 20200416

ACTIVE INGREDIENTS: ALCOHOL 0.93 mL/1.5 mL
INACTIVE INGREDIENTS: POLYOXYL 40 HYDROGENATED CASTOR OIL; ALOE VERA LEAF; GLYCERIN; CARBOMER HOMOPOLYMER, UNSPECIFIED TYPE; WATER; PANTHENOL; CHLORPHENESIN; HYDROXYETHYL CELLULOSE, UNSPECIFIED; TROLAMINE

Naisture Hand Sanitizer 1.5 ml x 100 : 75024-015-10